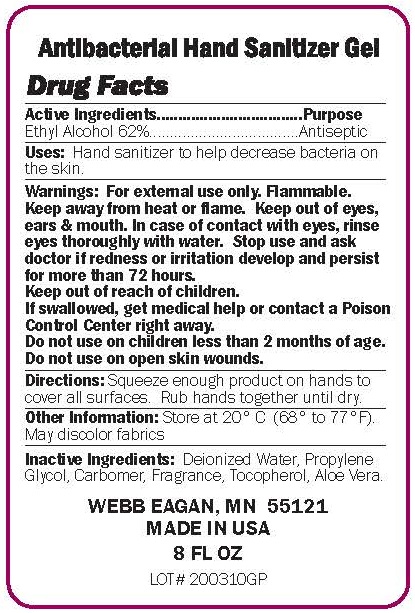 DRUG LABEL: Antibacterial Hand Sanitizer
NDC: 70445-411 | Form: GEL
Manufacturer: Webb Business Promotions, Incorporated
Category: otc | Type: HUMAN OTC DRUG LABEL
Date: 20220104

ACTIVE INGREDIENTS: ALCOHOL 62 mL/100 mL
INACTIVE INGREDIENTS: PROPYLENE GLYCOL; CARBOMER HOMOPOLYMER, UNSPECIFIED TYPE; WATER; TOCOPHEROL; ALOE VERA LEAF

ANTIBACTERIAL HAND SANITIZER GEL

Active Ingredient(s)

ETHYL ALCOHOL 62%

Purpose

Antiseptic

Use

HAND SANITIZER TO HELP DECREASE BACTERIA ON THE SKIN. WHEN WATER, SOAP & TOWEL ARE NOT AVAILABLE. RECOMMENDED FOR REPEATED USE.

Keep out of reach of children. Children must be supervised in use of this product.

Directions

SQUIRT AS NEEDED INTO PALMS AND THOROUGHLY SPREAD ON BOTH HANDS. RUB INTO SKIN UNTIL DRY.

Other information

Store at 20°C (68°- 77°F). May discolor fabrics

Inactive ingredients

WATER, PROPYLENE GLYCOL, CARBOMER, TRIETHANOLAMINE, FRAGRANCE, TOCOPHEROL, ALOE VERA